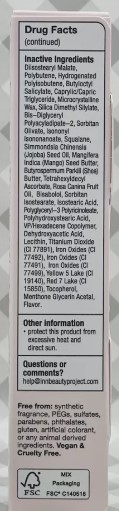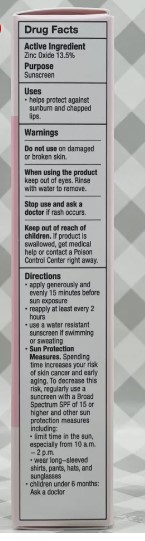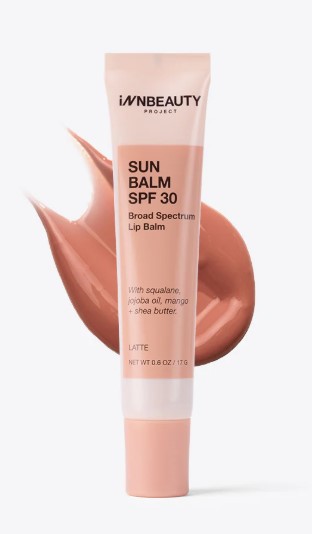 DRUG LABEL: INN BEAUTY SUN BALM SPF30 BROAD SPECTRUM LIP BALM - LATTE
NDC: 68577-193 | Form: CREAM
Manufacturer: COSMAX USA, CORPORATION
Category: otc | Type: HUMAN OTC DRUG LABEL
Date: 20241220

ACTIVE INGREDIENTS: ZINC OXIDE 13.5 mg/1 g
INACTIVE INGREDIENTS: SILICA DIMETHYL SILYLATE; TOCOPHEROL; IRON OXIDES; MENTHONE GLYCERIN ACETAL; POLYBUTENE (1400 MW); ISONONYL ISONONANOATE; SQUALANE; ISOSTEARIC ACID; DIISOSTEARYL MALATE; BUTYLOCTYL SALICYLATE; CAPRYLIC/CAPRIC TRIGLYCERIDE; BIS-DIGLYCERYL POLYACYLADIPATE-2; SIMMONDSIA CHINENSIS (JOJOBA) SEED OIL; POLYGLYCERYL-3 PENTARICINOLEATE; BUTYROSPERMUM PARKII (SHEA) BUTTER; ROSA CANINA FRUIT OIL; SORBITAN ISOSTEARATE; VP/HEXADECENE COPOLYMER; DEHYDROACETIC ACID; MICROCRYSTALLINE WAX; TITANIUM DIOXIDE; TETRAHEXYLDECYL ASCORBATE; POLYHYDROXYSTEARIC ACID (2300 MW); SORBITAN OLIVATE; MANGIFERA INDICA (MANGO) SEED BUTTER; HYDROGENATED POLYISOBUTENE (450 MW); BISABOLOL

INN BEAUTY SUN BALM SPF30 BROAD SPECTRUM LIP BALM - LATTE

Active Ingredient

Zinc Oxide 13.5%

Purpose

Sunscreen

USES

- helps protect against sunburn and chapped lips

WARNINGS

Do not useon damaged or broken skin

WHEN USING

When using the productkeep out of eyes. Rinse with water to remove.

Stop use and ask a doctorif rash occurs

Keep out of reach of children.If product is swallowed, get medical help or contact a Poison Control center right away.

DIRECTIONS

- apply generously and evenly 15 minutes before sun exposure
- reapply at least every 2 hours
- use a water resistant sunscreen if swimming or sweating

Sun Protection Measures. Spending time increases your risk of skin cancer and early aging. To decrease this risk, regularly use a sunscreen with a Broad Spectrum SPF of 15 or higher and other sun protection measures indluding:

- limit time in the sun, especially from 10 a.m. - 2 p.m.
- wear long-sleeved shirts, pants, hats, and sunglasses
- children under 6 months: Ask a doctor

Inactive Ingredients:

Diisostearyl Malate, Polybutene, Hydrogenated Polyisobutene, Butyloctyl Salicylate, Caprylic/Capric Triglyceride, Microcrystalline Wax, Silica Dimethyl Silylate, Bis-Diglyceryl Polyacyladipate-2, Sorbitan Olivate, Isononyl Isononanoate, Squalane, Simmondsia Chinensis (Jojoba) Seed Oil, Mangifera Indica (Mango) Seed Butter, Butyrospermum Parkiii (Shea) Butter, Tetrahexyldecyl Ascorbate, Rosa Canina Fruit Oil, Bisabolol, Sorbitan Isostearate, Isostearic Acid, Polyglyceryl-3 Polyricinoleate, Polyhydroxystearic Acid, VP/Hexadecene Copolymer, Dehydroxyacetic Acid, Lecithin, Titanium Dioxide (CI 77891), Iron Oxides (CI 77492), Iron Oxides (CI 77491), Iron Oxides (CI 77499), Yellow 5 Lake (CI 19140), Red 7 Lake (CI 15850), Tocopherol, Menthone Glycerin Acetal, Flavor.

OTHER INFORMATION

- protect this product from excessive heat and direct sun